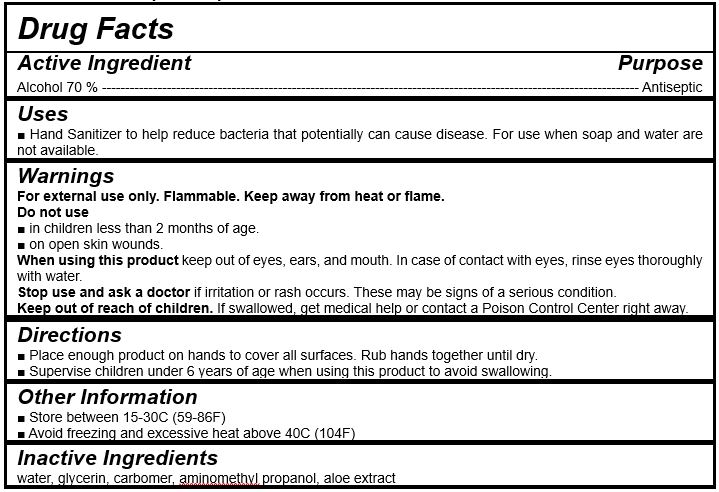 DRUG LABEL: Medicare Hand Sanitizer
NDC: 75363-0004 | Form: GEL
Manufacturer: Korea Medicare Co., Ltd.
Category: otc | Type: HUMAN OTC DRUG LABEL
Date: 20220106

ACTIVE INGREDIENTS: ALCOHOL 350 mL/500 mL
INACTIVE INGREDIENTS: WATER; GLYCERIN; CARBOMER HOMOPOLYMER, UNSPECIFIED TYPE; AMINOMETHYLPROPANOL; ALOE

Korea Medicare Co., Ltd. - Medicare Hand Sanitizer

ACTIVE INGREDIENT

Alcohol

INACTIVE INGREDIENT

water, etc

PURPOSE

Hand sanitizer to help reduce bacteria that potentially can cause disease. For use when soap and water are not available.

keep out of reach of the children

INDICATIONS AND USAGE

Place enough product on hands to cover all surfaces. Rub hands together until dry.

Supervise children under 6 years of age when using this product to avoid swallowing.

WARNINGS

For external use only. Flammable. Keep away from heat or flame.

Do not use

- in children less than 2 months of age
- on open skin wounds

When using this product keep out of eyes, ears, and mouth. In case of contact with eyes, rinse thoroughly with water.

Stop use and ask a doctor if irritation or rash occurs. These may be signs of a serious condition.

Keep out of reach of children. If swallowed, get medical help or contact a Poison Control Center right away.

DOSAGE AND ADMINISTRATION

for external use only